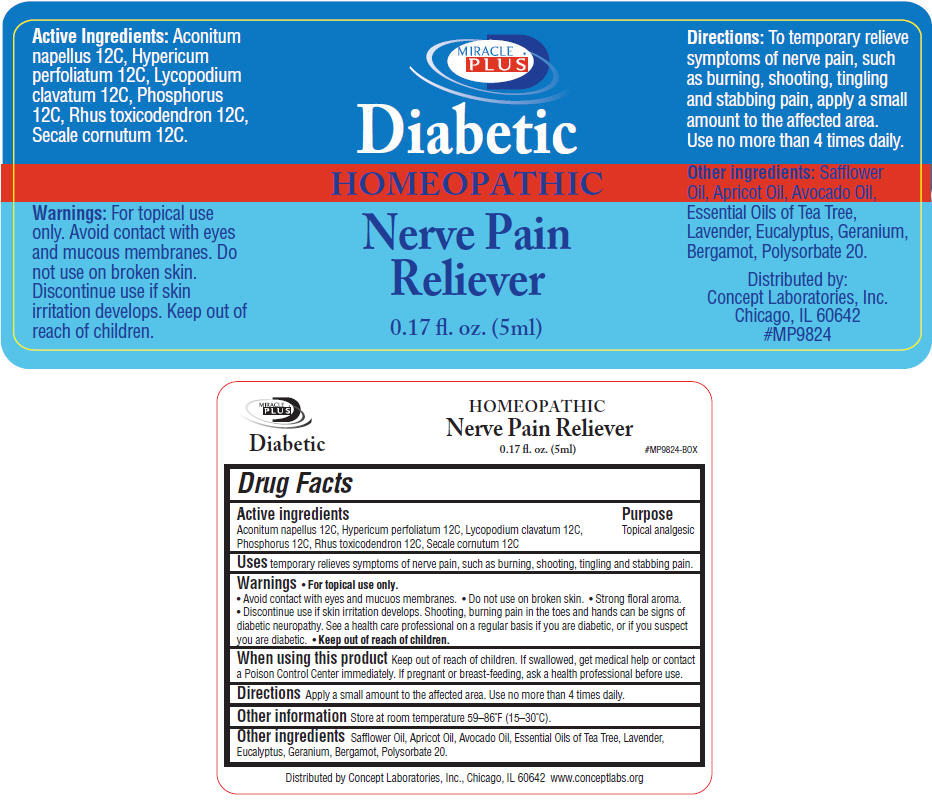 DRUG LABEL: Miracle Plus Diabetic Homeopathic
NDC: 64058-145 | Form: LIQUID
Manufacturer: Concept Laboratories, Inc.
Category: homeopathic | Type: HUMAN OTC DRUG LABEL
Date: 20191115

ACTIVE INGREDIENTS: ACONITUM NAPELLUS 12 [hp_C]/5 mL; HYPERICUM PERFORATUM 12 [hp_C]/5 mL; LYCOPODIUM CLAVATUM SPORE 12 [hp_C]/5 mL; PHOSPHORUS 12 [hp_C]/5 mL; TOXICODENDRON PUBESCENS LEAF 12 [hp_C]/5 mL; CLAVICEPS PURPUREA SCLEROTIUM 12 [hp_C]/5 mL
INACTIVE INGREDIENTS: POLYSORBATE 20; SAFFLOWER OIL; APRICOT KERNEL OIL; AVOCADO OIL; TEA TREE OIL; LAVENDER OIL; EUCALYPTUS OIL; GERANIUM OIL, ALGERIAN TYPE; BERGAMOT OIL

Miracle Plus® Diabetic Homeopathic
Nerve Pain Reliever

Drug Facts

Active ingredients

Aconitum napellus 12C, Hypericum perfoliatum 12C, Lycopodium clavatum 12C, Phosphorus 12C, Rhus toxicodendron 12C, Secale cornutum 12C

Purpose

Topical analgesic

Uses

temporary relieves symptoms of nerve pain, such as burning, shooting, tingling and stabbing pain.

Warnings

- For topical use only.

WHEN USING

- Avoid contact with eyes and mucuos membranes.

- Do not use on broken skin.
- Strong floral aroma.

STOP USE

- Discontinue use if skin irritation develops. Shooting, burning pain in the toes and hands can be signs of diabetic neuropathy.

ASK DOCTOR

See a health care professional on a regular basis if you are diabetic, or if you suspect you are diabetic.

- Keep out of reach of children.

When using this product Keep out of reach of children. If swallowed, get medical help or contact a Poison Control Center immediately.

PREGNANCY OR BREAST FEEDING

If pregnant or breast-feeding, ask a health professional before use.

Directions

Apply a small amount to the affected area. Use no more than 4 times daily.

Other information

Store at room temperature 59–86°F (15–30°C).

Other ingredients

Safflower Oil, Apricot Oil, Avocado Oil, Essential Oils of Tea Tree, Lavender, Eucalyptus, Geranium, Bergamot, Polysorbate 20.

Distributed by Concept Laboratories, Inc., Chicago, IL 60642 www.conceptlabs.org

PRINCIPAL DISPLAY PANEL - 5 mL Bottle Label

Miracle Plus®

Diabetic Homeopathic Nerve Pain Reliever

0.17 fl oz (5 ml)